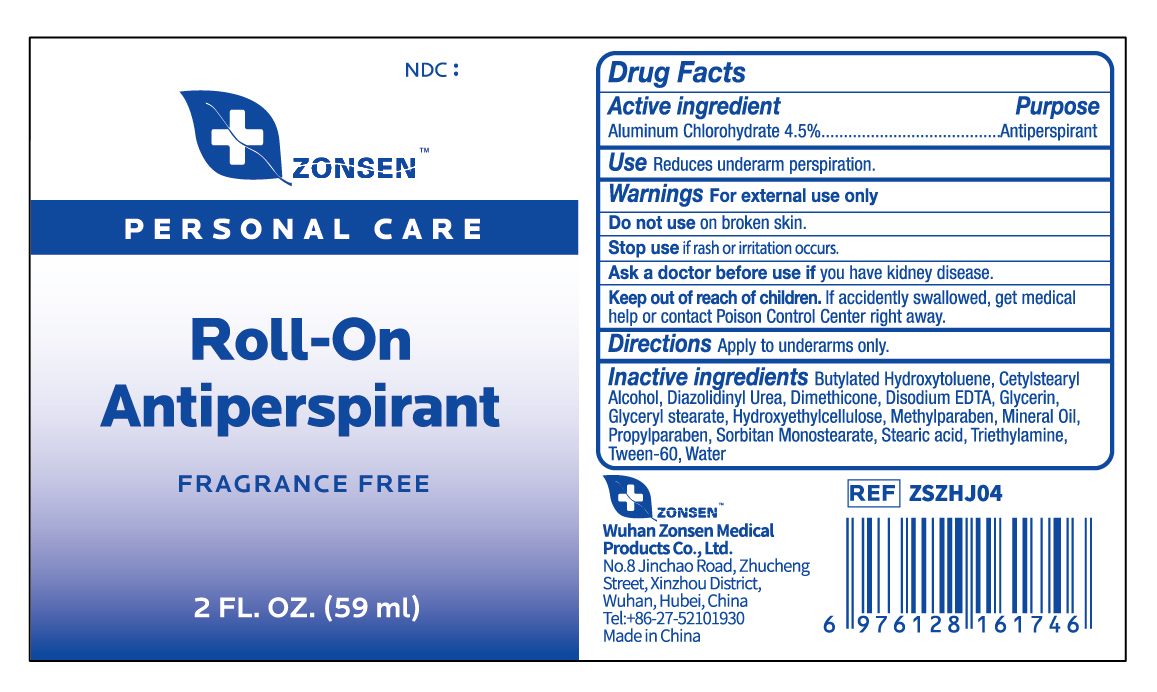 DRUG LABEL: ZONSEN Roll-On Antiperspirant
NDC: 72932-013 | Form: LOTION
Manufacturer: Wuhan Zonsen Medical Products Co., Ltd.
Category: otc | Type: HUMAN OTC DRUG LABEL
Date: 20240821

ACTIVE INGREDIENTS: ALUMINUM CHLOROHYDRATE 45 mg/1 mL
INACTIVE INGREDIENTS: DIMETHICONE; TRIETHYLAMINE; CETOSTEARYL ALCOHOL; SORBITAN MONOSTEARATE; MINERAL OIL; GLYCERYL MONOSTEARATE; EDETATE DISODIUM; DIAZOLIDINYL UREA; METHYLPARABEN; POLYSORBATE 60; WATER; GLYCERIN; PROPYLPARABEN; STEARIC ACID; HYDROXYETHYL CELLULOSE, UNSPECIFIED; BUTYLATED HYDROXYTOLUENE

Active Ingredient

Aluminum Chlorohydrate 4.5%

PURPOSE

Antiperspirant

USE

Reduces underarm perspiration.

Warnings

For external use only

DO NOT USE

on broken skin.

STOP USE

if rash or irritation occurs.

Ask Doctor before use

if you have kidney disease.

Keep out of reach of children

■If accidently swallowed, get medical help or contact Poison Control Center right away

Directions

Apply to underarms only.

Inactive Ingredient

Water, Stearic acid, Mineral Oil, Sorbitan Monostearate, Cetylstearyl Alcohol, Dimethicone, Glyceryl stearate, Butylated Hydroxytoluene, Methyl paraben, Propylparaben, Glycerin, Hydroxyethyl cellulose, Disodium EDTA, Tween-60, Triethylamine, Diazolidinyl Urea

DOSAGE & ADMINISTRATION

Use daily for best results.